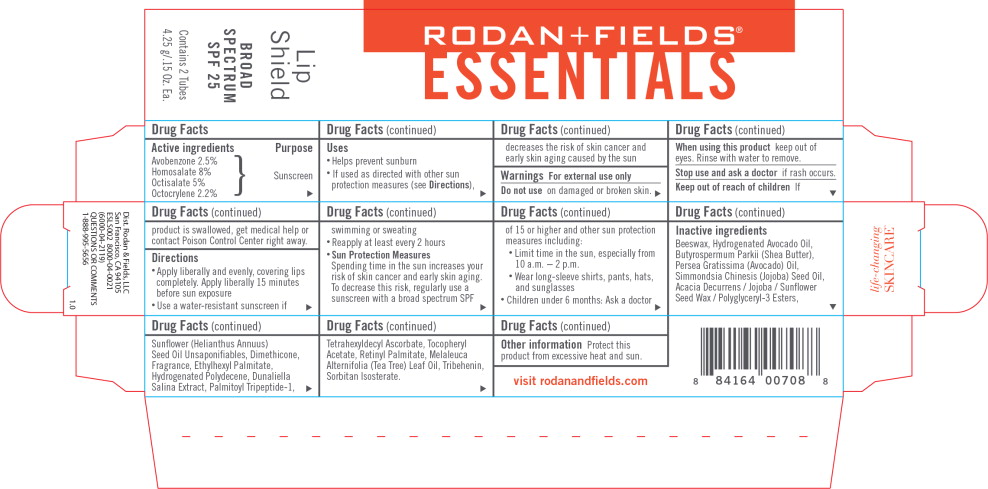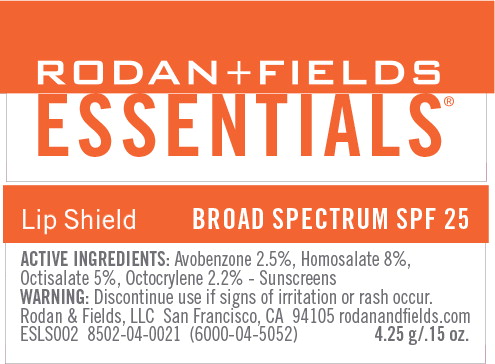 DRUG LABEL: Rodan and Fields ESSENTIALS Lip Shield Broad Spectrum SPF 25
NDC: 14222-0425 | Form: STICK
Manufacturer: Rodan & Fields
Category: otc | Type: HUMAN OTC DRUG LABEL
Date: 20231212

ACTIVE INGREDIENTS: AVOBENZONE 2.5 g/100 g; HOMOSALATE 8 g/100 g; OCTISALATE 5 g/100 g; OCTOCRYLENE 2.2 g/100 g
INACTIVE INGREDIENTS: YELLOW WAX; HYDROGENATED AVOCADO OIL; SHEA BUTTER; AVOCADO OIL; JOJOBA OIL; DIMETHICONE; ETHYLHEXYL PALMITATE; HYDROGENATED POLYDECENE (550 MW); DUNALIELLA SALINA; PALMITOYL TRIPEPTIDE-1; TETRAHEXYLDECYL ASCORBATE; .ALPHA.-TOCOPHEROL ACETATE; VITAMIN A PALMITATE; TEA TREE OIL; TRIBEHENIN; SORBITAN ISOSTEARATE

Drug Facts

Active Ingredients

Avobenzone 2.5%

Homosalate 8%

Octisalate 5%

Octocrylene 2.2%

Purpose

Sunscreen

Uses

- Helps prevent sunburn
- If used as directed with other sun protection measures (See), decreases the risk of skin cancer and early skin aging caused by the sun Directions

Warnings For external use only

on damaged or broken skin. Do not use

WHEN USING

keep out of eyes. Rinse with water to remove. When using this product

STOP USE

if rash occurs. Stop use and ask a doctor

KEEP OUT OF REACH OF CHILDREN

If product is swallowed, get medical help or contact Poison Control Center right away. Keep out of reach of Children

Directions

- Apply liberally and evenly, covering lips completely. Apply liberally 15 minutes before sun exposure
- Use a water-resistant sunscreen if swimming or sweating
- Reapply at least every 2 hours
- Sun Protection Measures
- Spending time in the sun increases your risk of skin cancer and early skin aging.
- To decrease this risk, regularly use a sunscreen with a broad spectrum SPF of 15 or higher and other sun protection measures including:
  - Limit time in the sun, especially from 10 a.m. - 2 p.m.
  - Wear long-sleeve shirts, pants, hats, and sunglasses
- Children under 6 months: Ask a doctor

Inactive ingredients

Beeswax, Hydrogenated Avocado Oil, Butyrospermum Parkii (Shea Butter), Persea Gratissima (Avocado) Oil, Simmondsia Chinesis (Jojoba) Seed Oil, Acacia Decurrens / Jojoba / Sunflower Seed Wax / Polyglyceryl-3 Esters, Sunflower (Helianthus Annuus) Seed Oil Unsaponifiables, Dimethicone, Fragrance, Ethylhexyl Palmitate, Hydrogenated Polydecene, Dunaliella Salina Extract, Palmitoyl Tripeptide-1, Tetrahexyldecyl Ascorbate, Tocopheryl Acetate, Retinyl Palmitate, Melaleuca Alternifolia (Tea Tree) Leaf Oil, Tribehenin, Sorbitan Isosterate.

Other information

Protect this product from excessive heat and sun.

Principal Display Panel - Essentials Lip Shield Outer Label

RODAN+FIELDS®

ESSENTIALS

Lip Shield

BROAD SPECTRUM SPF 25

Contains 2 Tubes

4.25 g/.15 Oz. Ea.

Principal Display Panel - Essentials Lip Shield Primary Label

RODAN+FIELDS®

ESSENTIALS